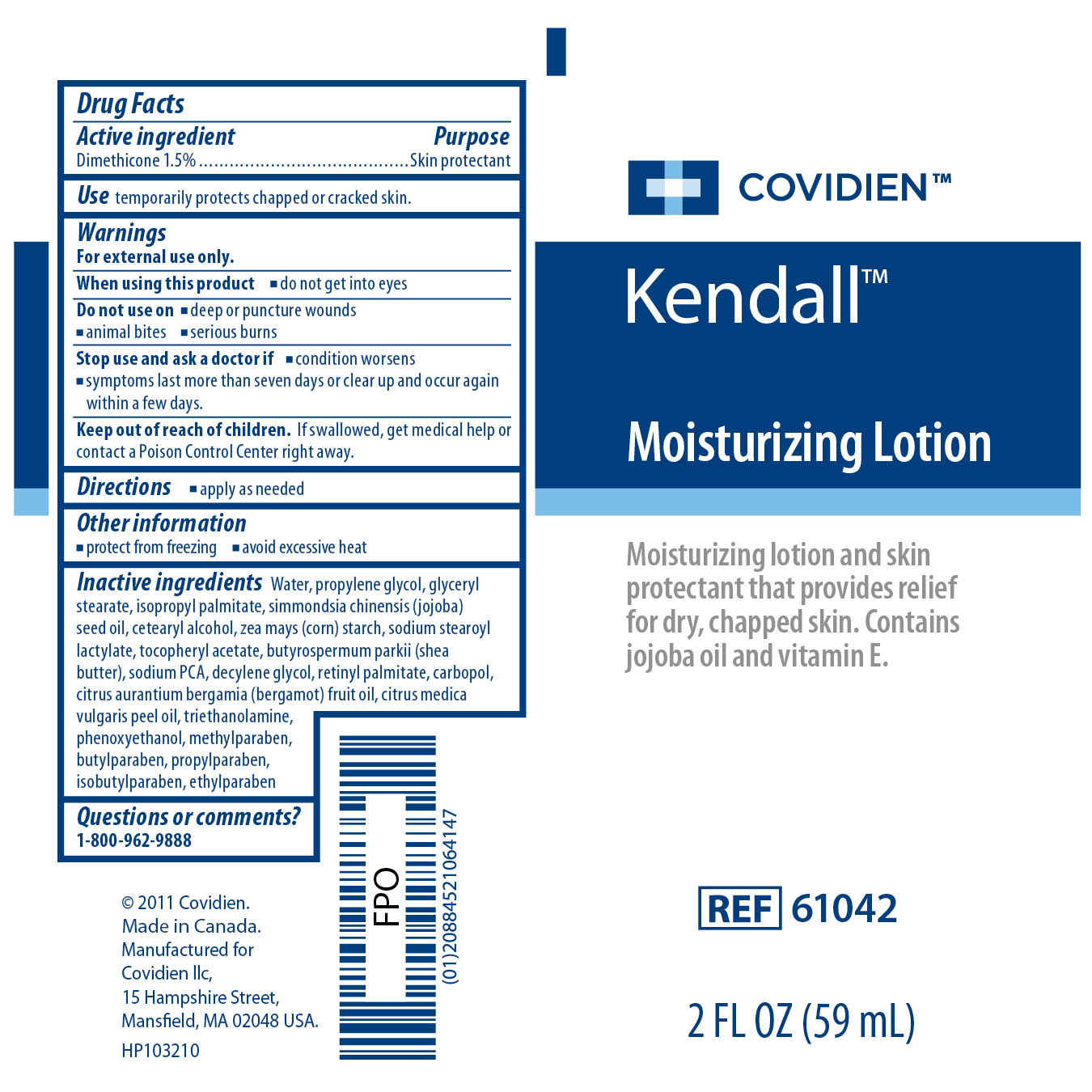 DRUG LABEL: Kendall Moisturizing
NDC: 28851-694 | Form: LOTION
Manufacturer: Covidien Inc.
Category: otc | Type: HUMAN OTC DRUG LABEL
Date: 20110427

ACTIVE INGREDIENTS: Dimethicone 1.5 mL/100 mL
INACTIVE INGREDIENTS: Water; JOJOBA OIL; STARCH, CORN; PROPYLENE GLYCOL ; GLYCERYL MONOSTEARATE; CETOSTEARYL ALCOHOL; SODIUM STEAROYL LACTYLATE; ISOPROPYL PALMITATE; PHENOXYETHANOL; BERGAMOT OIL ; TROLAMINE; VITAMIN A PALMITATE; CARBOMER 1342; SODIUM PYRROLIDONE CARBOXYLATE; 1-DECENE; METHYLPARABEN; BUTYLPARABEN; PROPYLPARABEN ; ISOBUTYLPARABEN; ETHYLPARABEN; SHEA BUTTER; ACETATE ION

Kendall Moisturizing Lotion

Active Ingredient

Dimethicone 1.5%

Purpose

Skin Protectant

Use

temporarily protects chapped or cracked skin.

Warnings

For external use only.
When using this product

- do not get into eyes

Do not use on

- deep or puncture wounds
- animal bites
- serious burns

Stop use and ask a doctor if

- condition worsens
- symptoms last more than seven days or clear up and occur again within a few days

Keep out of the reach of children. If swallowed, get medical help or contact a Poison Control Center right away.

Directions

- apply as needed

Other Information

- protect from freezing
- avoid excessive heat

Inactive ingredients

Water, simmondsia chinensis (jojoba) seed oil, zea mays (corn) starch, cetearyl alcohol, glyceryl stearate, cirtus aurantium bergamia (bergamot) fruit oil, citrus medica vulgaris peel oil, sodium stearoyl lactylate, retinyl palmitate, tocopheryl acetate, isopropyl palmitate, propylene glycol, triethanolamine, sodium PCA, carbopol, butyrospermum parkii (shea butter), decylene glycol, phenoxyethanol, methylparaben, butylparaben, propylparaben, isobutylparaben, ethylparaben

Questions or comments? 1-800-962-9888

PACKAGE LABEL

Image of Kendall Moisturizing Lotion 2 Fl oz Label